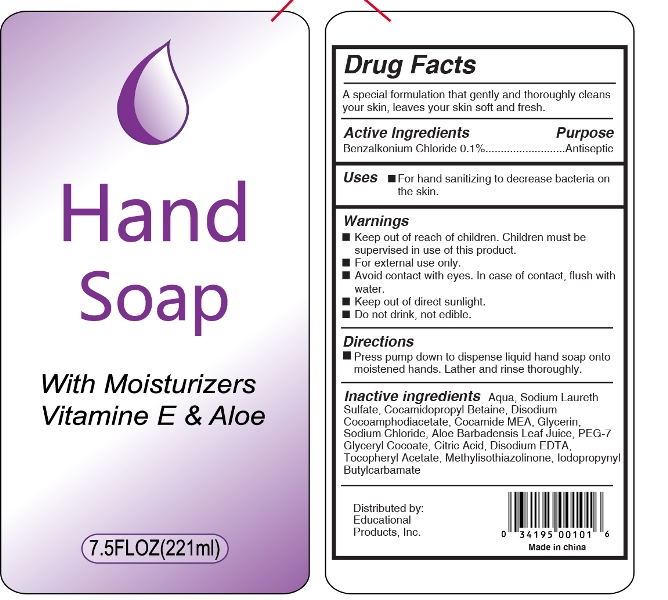 DRUG LABEL: antibacterial hand sanitizer
NDC: 61312-007 | Form: GEL
Manufacturer: Hangzhou  Guoguang  Touring  Commodity  Co., Ltd.
Category: otc | Type: HUMAN OTC DRUG LABEL
Date: 20180106

ACTIVE INGREDIENTS: BENZALKONIUM CHLORIDE 0.1 g/100 g
INACTIVE INGREDIENTS: WATER; GLYCERIN; SODIUM LAURETH SULFATE; SODIUM CHLORIDE; DISODIUM COCOAMPHODIACETATE; COCAMIDE; ALOE VERA LEAF; GLYCERYL COCOATE; CITRIC ACID ACETATE; DISODIUM EDTA-COPPER; TOCOPHERYL RETINOATE; METHYLISOTHIAZOLINONE; IODOPROPYNYL BUTYLCARBAMATE

Hand Soap

Active Ingredient

Benzalkonium chloride 0.1%

Purpose

Antispetic

Use

for hand washing to decrease bacteria on skin

WARNINGS

For External use only-hands.

Avoid contact with eyes,in case of contact ,flush with water.

Keep out of direct sunlight

do not drink,not edible

keep out of reach of children

Directions

press pump down to dispense liquid hand soap onto moistened hands,lather and rinse thoroughly

Inactive ingredients

aqua ,sodium laureth sulfate,cocamidopropyl betaine,disodium cocoamphodiacetate,cocamide MEDA,Glycerin,Aloe Barbadensis leaf juice,PEG-7 glyceryl cocoate,sodium chloride,citric acid ,disodium EDTA,tocopheryl acetate,methylisothiazolinone,lodopropynyl butylcarbamate